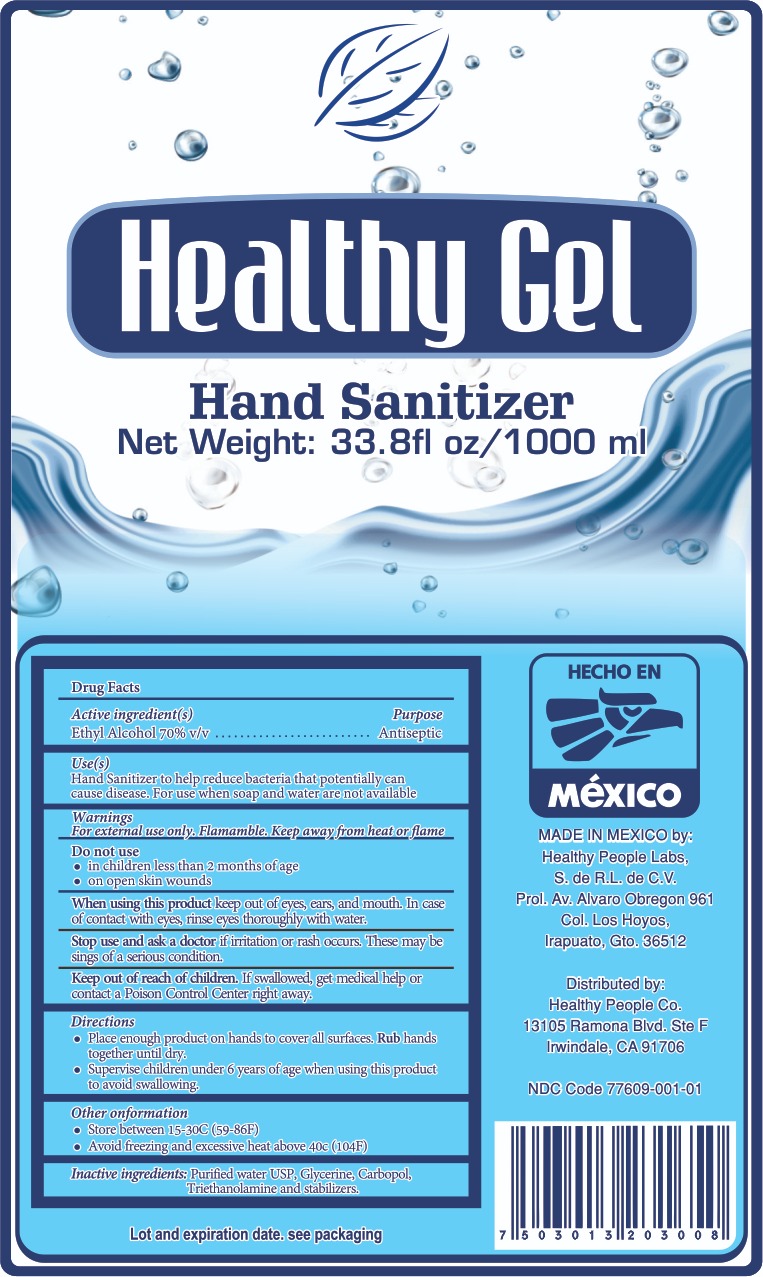 DRUG LABEL: Hand Sanitizer
NDC: 77609-001 | Form: GEL
Manufacturer: Healthy People Co
Category: otc | Type: HUMAN OTC DRUG LABEL
Date: 20200610

ACTIVE INGREDIENTS: ALCOHOL 70 mL/100 mL
INACTIVE INGREDIENTS: GLYCERIN 2 mL/100 mL; CARBOMER 940 0.35 mL/100 mL; WATER; TROLAMINE 0.1 mL/100 mL

Hand Sanitizer

This is a hand sanitizer manufactured using only the following United States Pharmacopoeia (USP) grade ingredients:

1. Alcohol (ethanol) (USP or Food Chemical Codex (FCC) grade) (70%, volume/volume (v/v)) in an aqueous solution denatured according to Alcohol and Tobacco Tax and Trade Bureau regulations in 27 CFR part 20.
2. Glycerin (2% v/v).
3. Carbopol (0.35% v/v).
4. Triethanolamine (.1% v/v).
5. Sterile distilled water or boiled cold water.

Active Ingredient(s)

Ethyl Alcohol 70% v/v. Purpose: Antiseptic

Purpose

Antiseptic, Hand Sanitizer

Use

Hand Sanitizer to help reduce bacteria that potentially can cause disease. For use when soap and water are not available.

Warnings

For external use only. Flammable. Keep away from heat or flame

Do not use

- in children less than 2 months of age
- on open skin wounds

When using this product keep out of eyes, ears, and mouth. In case of contact with eyes, rinse eyes thoroughly with water.
Stop use and ask a doctor if irritation or rash occurs. These may be signs of a serious condition.
Keep out of reach of children. If swallowed, get medical help or contact a Poison Control Center right away.

Stop use and ask a doctor if irritation or rash occurs. These may be signs of a serious condition.

Keep out of reach of children. If swallowed, get medical help or contact a Poison Control Center right away.

Directions

- Place enough product on hands to cover all surfaces. Rub hands together until dry.
- Supervise children under 6 years of age when using this product to avoid swallowing.

Other information

- Store between 15-30C (59-86F)
- Avoid freezing and excessive heat above 40C (104F)

Inactive ingredients

Purified water USP, Glycerine, Carbopol, Triethanolamine, and stabilizers.

Package Label - Principal Display Panel

1000 mL NDC: 77609-001-01